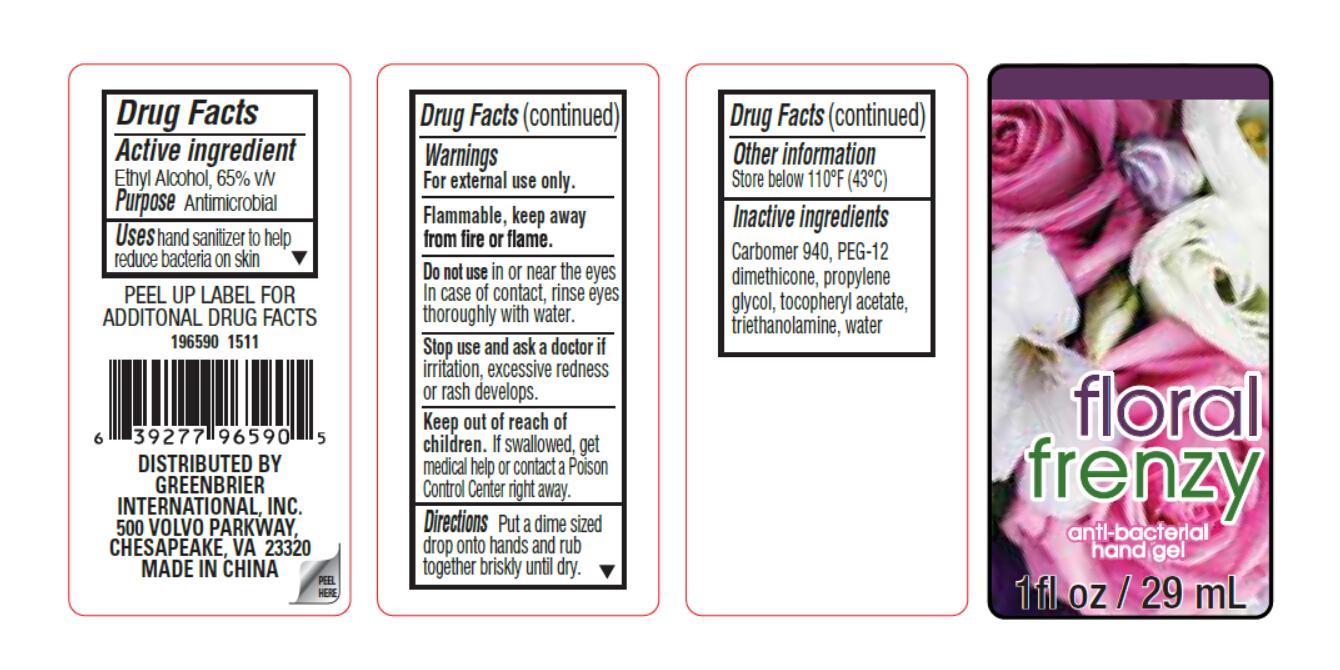 DRUG LABEL: floral frenzy
NDC: 58194-027 | Form: GEL
Manufacturer: Shanghai Weierya Daily Chemicals Factory
Category: otc | Type: HUMAN OTC DRUG LABEL
Date: 20150703

ACTIVE INGREDIENTS: ALCOHOL 65 mL/100 mL
INACTIVE INGREDIENTS: CARBOMER HOMOPOLYMER TYPE C (ALLYL PENTAERYTHRITOL CROSSLINKED); PEG-12 DIMETHICONE (300 CST); PROPYLENE GLYCOL; .ALPHA.-TOCOPHEROL ACETATE; TROLAMINE; WATER

Drug Facts

Inactive Ingredients

carbomer 940,

PEG-12 dimethicone,

propylene glycol,

tocopheryl acetate,

triethanolamine,

water

Active Ingredient

Ethyl Alcohol 65 % v/v

Purpose Antimicrobial

Warnings

For external use only.

Keep out of reach of children. If swallowed,

get medical help or contact a Poison

Control Center right away.

Uses

hand sanitizer to help reduce bacteria on skin

DOSAGE AND ADMINISTRATION

Directions Put a dime sized drop onto hands

and rub together briskly until dry.

Do not use in or near the eyes.

In case of contact, rinse eyes

thoroughly with water.

Stop use and ask a doctor

if irritation, excessive redness or

rash develops.

OTHER SAFETY INFORMATION

Flammable. Keep away from

fire or flame.

Other Information

Store below 110 F (43 C)